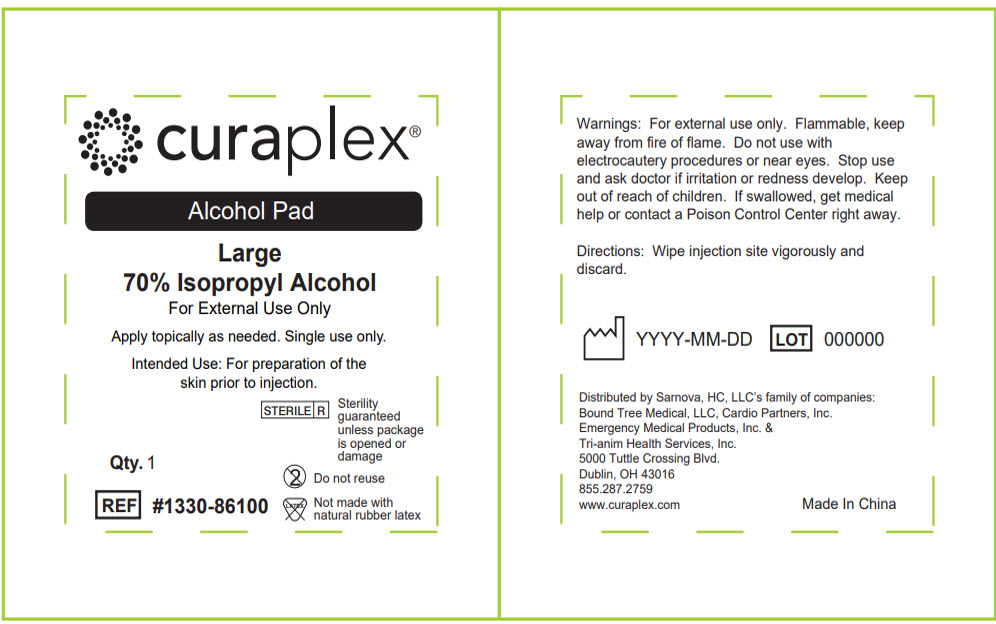 DRUG LABEL: Isopropyl Alcohol
NDC: 81085-0002 | Form: CLOTH
Manufacturer: Sarnova, Inc.
Category: otc | Type: HUMAN OTC DRUG LABEL
Date: 20241206

ACTIVE INGREDIENTS: ISOPROPYL ALCOHOL 70 mL/100 mL
INACTIVE INGREDIENTS: WATER

Isopropyl Alcohol

ACTIVE INGREDIENT

70% Isopropyl Alcohol

INDICATIONS AND USAGE

Apply topically as needed. Single use only.

Intended Use

For preparation of the skin prior to injection.

Warnings

For external use only. Flammable, keep away from fire of flame. Do not use with electrocautery procedures or near eyes. Stop use and ask doctor if irritation or redness develop.

Keep out of reach of children. If swallowed, get medical help or contact a Poison Control Center right away.

Directions

Wipe injection site vigorously and discard.

Inactive ingredients

Purified water

Distributed by Sarnova, HC, LLC's family of companies:
Bound Tree Medical, LLC, Cardio Partners, Inc.
Emergency Medical Products, Inc. &
Tri-anim Health Services, Inc.
5000 Tuttle Crossing Blvd.
Dublin, OH 43016

PRINCIPAL DISPLAY PANEL - 0.4 mL Pouch Label

curaplex®

Alcohol Pad

Large
70% Isopropyl Alcohol

For External Use Only

Apply topically as needed. Single use only.

Intended Use: For preparation of the
skin prior to injection.

Qty. 1

STERILE R

Sterility
guaranteed
unless package
is opened or
damage

Do not reuse

REF #1330-86100

Not made with
natural rubber latex